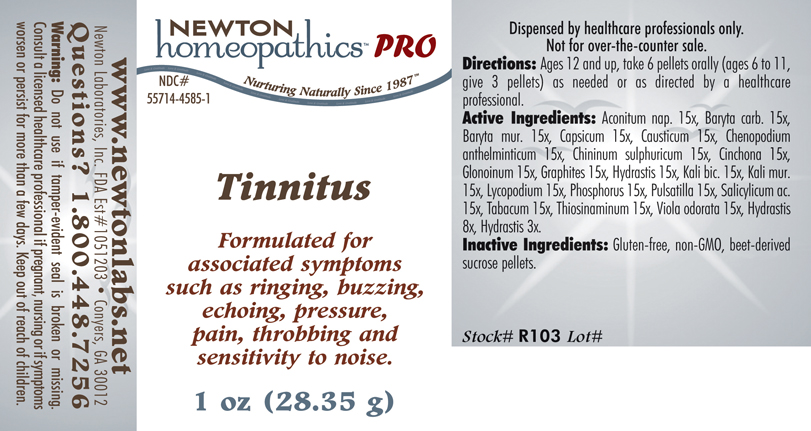 DRUG LABEL: Tinnitus 
NDC: 55714-4585 | Form: PELLET
Manufacturer: Newton Laboratories, Inc.
Category: homeopathic | Type: HUMAN PRESCRIPTION DRUG LABEL
Date: 20110601

ACTIVE INGREDIENTS: Aconitum Napellus 15 [hp_X]/1 g; Barium Carbonate 15 [hp_X]/1 g; Barium Chloride Dihydrate 15 [hp_X]/1 g; Capsicum 15 [hp_X]/1 g; Causticum 15 [hp_X]/1 g; Dysphania Ambrosioides 15 [hp_X]/1 g; Quinine Sulfate 15 [hp_X]/1 g; Cinchona Officinalis Bark 15 [hp_X]/1 g; Nitroglycerin 15 [hp_X]/1 g; Graphite 15 [hp_X]/1 g; Goldenseal 15 [hp_X]/1 g; Potassium Dichromate 15 [hp_X]/1 g; Potassium Chloride 15 [hp_X]/1 g; Lycopodium Clavatum Spore 15 [hp_X]/1 g; Phosphorus 15 [hp_X]/1 g; Pulsatilla Vulgaris 15 [hp_X]/1 g; Salicylic Acid 15 [hp_X]/1 g; Tobacco Leaf 15 [hp_X]/1 g; Allylthiourea 15 [hp_X]/1 g; Viola Odorata 15 [hp_X]/1 g
INACTIVE INGREDIENTS: Sucrose

Tinnitus

INDICATIONS & USAGE SECTION

Tinnitus Formulated for associated symptoms such as ringing, buzzing, echoing, pressure, pain, throbbing and sensitivity to noise.

DOSAGE & ADMINISTRATION SECTION

Directions: Ages 12 and up, take 6 pellets orally (ages 6 to 11, give 3 pellets) as needed or as directed by a healthcare professional.

ACTIVE INGREDIENT SECTION

Aconitum nap. 15x, Baryta carb. 15x, Baryta mur. 15x, Capsicum 15x, Causticum 15x, Chenopodium anthelminticum 15x, Chininum sulphuricum 15x, Cinchona 15x, Glonoinum 15x, Graphites 15x, Hydrastis 15x, Kali bic. 15x, Kali mur.15x, Lycopodium 15x, Phosphorus 15x, Pulsatilla 15x, Salicylicum ac.15x, Tabacum 15x, Thiosinaminum 15x, Viola odorata 15x, Hydrastis 8x, Hydrastis 3x.

PURPOSE SECTION

Formulated for associated symptoms such as ringing, buzzing, echoing, pressure, pain, throbbing and sensitivity to noise.

INACTIVE INGREDIENT SECTION

Inactive Ingredients: Gluten-free, non-GMO, beet-derived sucrose pellets.

QUESTIONS? SECTION

www.newtonlabs.net Newton Laboratories, Inc. FDA Est # 1051203 - Conyers, GA 30012
Questions? 1.800.448.7256

WARNINGS SECTION

Warning: Do not use if tamper - evident seal is broken or missing. Consult a licensed healthcare professional if pregnant, nursing or if symptoms worsen or persist for more than a few days. Keep out of reach of children.

PREGNANCY OR BREAST FEEDING SECTION

Consult a licensed healthcare professional if pregnant, nursing or if symptoms worsen or persist for more than a few days.

KEEP OUT OF REACH OF CHILDREN SECTION

Keep out of reach of children